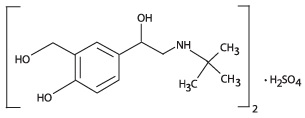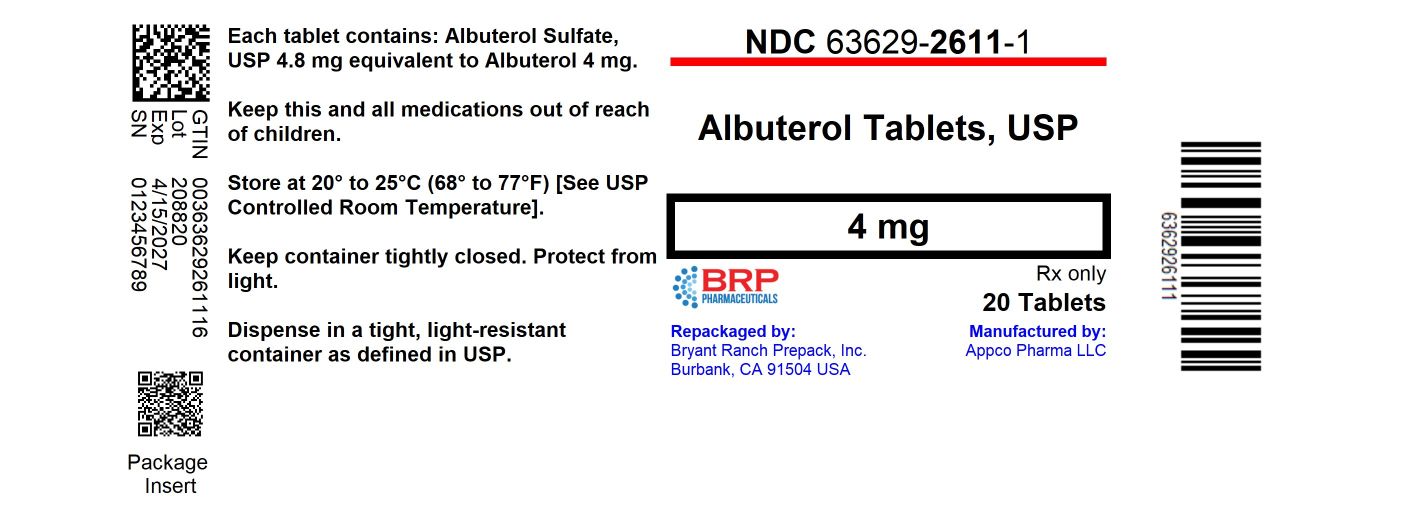 DRUG LABEL: Albuterol
NDC: 63629-2611 | Form: TABLET
Manufacturer: Bryant Ranch Prepack
Category: prescription | Type: HUMAN PRESCRIPTION DRUG LABEL
Date: 20250421

ACTIVE INGREDIENTS: ALBUTEROL SULFATE 4 mg/1 1
INACTIVE INGREDIENTS: LACTOSE, UNSPECIFIED FORM; MAGNESIUM STEARATE; STARCH, CORN; SODIUM LAURYL SULFATE

Albuterol Tablets, USP
Rx only

DESCRIPTION

Albuterol Tablets, USP contain albuterol sulfate, USP the racemic form of albuterol and a relatively selective beta2-adrenergic bronchodilator.

Albuterol sulfate has the chemical name 4-hydroxy- 3-hydroxymethyl-α-[(tert-butylamino) methyl]benzyl alcohol, sulfate and the following structural formula:

The molecular weight of albuterol sulfate is 576, and the molecular formula is (C13 H21N O3)2• H2S O4. Albuterol sulfate is a white or practically white powder, freely soluble in water and slightly soluble in alcohol, in chloroform, and ether.

The World Health Organization recommended name for albuterol base is salbutamol.

Each Albuterol tablet for oral administration contains 2 or 4 mg of albuterol as 2.4 mg or 4.8 mg of albuterol sulfate, USP respectively.

The inactive ingredients for albuterol tablets, 2 mg and 4 mg include: co-processed starch, lactose hydrate, magnesium stearate, partially pregelatinized maize starch and sodium lauryl sulfate.

CLINICAL PHARMACOLOGY

In vitrostudies and in vivopharmacologic studies have demonstrated that albuterol has a preferential effect on beta2-adrenergic receptors compared with isoproterenol. While it is recognized that beta2-adrenergic receptors are the predominant receptors in bronchial smooth muscle, data indicate that there is a population of beta2-receptors in the human heart existing in a concentration between 10% and 50%. The precise function of these receptors has not been established (see WARNINGS).
The pharmacologic effects of beta-adrenergic agonist drugs, including albuterol tablets, are at least in part attributable to stimulation through beta-adrenergic receptors of intracellular adenyl cyclase, the enzyme that catalyzes the conversion of adenosine triphosphate (ATP) to cyclic-3',5'- adenosine monophosphate (cyclic AMP). Increased cyclic AMP levels are associated with relaxation of bronchial smooth muscle and inhibition of release of mediators of immediate hypersensitivity from cells, especially from mast cells.
Albuterol tablets have been shown in most controlled clinical trials to have more effect on the respiratory tract, in the form of bronchial smooth muscle relaxation, than isoproterenol at comparable doses while producing fewer cardiovascular effects.

Albuterol is longer acting than isoproterenol in most patients by any route of administration because it is not a substrate for the cellular uptake processes for catecholamines nor for catechol- O-methyl transferase.

Preclinical

Intravenous studies in rats with albuterol sulfate have demonstrated that albuterol crosses the blood brain barrier and reaches brain concentrations amounting to approximately 5% of the plasma concentrations. In structures outside the brain barrier (pineal and pituitary glands), albuterol concentrations were found to be 100 times those in the whole brain.

Studies in laboratory animals (minipigs, rodents, and dogs) have demonstrated the occurrence of cardiac arrhythmias and sudden death (with histologic evidence of myocardial necrosis) when beta-agonists and methylxanthines are administered concurrently. The clinical significance of these findings is unknown.

Pharmacokinetics

Albuterol tablets are rapidly absorbed after oral administration of one 4 mg albuterol tablet in normal volunteers. Maximum plasma concentrations of about 18 ng/mL of albuterol are achieved within 2 hours, and the drug is eliminated with a half-life of about 5 hours.

In other studies, the analysis of urine samples of patients given 8 mg of tritiated albuterol tablets orally showed that 76% of the dose was excreted over 3 days, with the majority of the dose being excreted within the first 24 hours. Sixty percent of this radioactivity was shown to be the metabolite. Feces collected over this period contained 4% of the administered dose.

Clinical Trials

In controlled clinical trials in patients with asthma, the onset of improvement in pulmonary function, as measured by maximum midexpiratory flow rate (MMEF), was noted within 30 minutes after a dose of Albuterol tablets, with peak improvement occurring between 2 and 3 hours. In controlled clinical trials in which measurements were conducted for 6 hours, clinically significant improvement (defined as maintaining a 15% or more increase in forced expiratory volume in 1 second [FEV1] and a 20% or more increase in MMEF over baseline values) was observed in 60% of patients at 4 hours and in 40% at 6 hours. In other single-dose, controlled clinical trials, clinically significant improvement was observed in at least 40% of the patients at 8 hours. No decrease in the effectiveness of albuterol tablets was reported in patients who received long-term treatment with the drug in uncontrolled studies for periods up to 6 months.

INDICATIONS & USAGE

Albuterol tablets are indicated for the relief of bronchospasm in adults and children 6 years of age and older with reversible obstructive airway disease.

CONTRAINDICATIONS

Albuterol tablets are contraindicated in patients with a history of hypersensitivity to albuterol, or any of its components.

WARNINGS

Paradoxical Bronchospasm

Albuterol tablets can produce paradoxical bronchospasm, which may be life threatening. If paradoxical bronchospasm occurs, albuterol tablets should be discontinued immediately and alternative therapy instituted.
Cardiovascular Effects
Albuterol tablets, like all other beta-adrenergic agonists, can produce a clinically significant cardiovascular effect in some patients as measured by pulse rate, blood pressure, and/or symptoms. Although such effects are uncommon after administration of albuterol tablets at recommended doses, if they occur, the drug may need to be discontinued. In addition, beta-agonists have been reported to produce electrocardiogram (ECG) changes, such as flattening of the T wave, prolongation of the QTc interval, and ST segment depression. The clinical significance of these findings is unknown. Therefore, albuterol tablets, like all sympathomimetic amines, should be used with caution in patients with cardiovascular disorders, especially coronary insufficiency, cardiac arrhythmias, and hypertension.

Deterioration of Asthma

Asthma may deteriorate acutely over a period of hours, or chronically over several days or longer. If the patient needs more doses of albuterol tablets than usual, this may be a marker of destabilization of asthma and requires reevaluation of the patient and the treatment regimen, giving special consideration to the possible need for anti-inflammatory treatment, e.g., corticosteroids.

Use of Anti-Inflammatory Agents

The use of beta-adrenergic agonist bronchodilators alone may not be adequate to control asthma in many patients. Early consideration should be given to adding anti-inflammatory agents, e.g., corticosteroids.

Immediate Hypersensitivity Reactions

Immediate hypersensitivity reactions may occur after administration of albuterol tablets, as demonstrated by rare cases of urticaria, angioedema, rash, bronchospasm and oropharyngeal edema. Albuterol tablets, like other beta-adrenergic agonists, can produce a significant cardiovascular effect in some patients, as measured by pulse rate, blood pressure, symptoms, and/or electrocardiographic changes.
Rarely, erythema multiforme and Stevens-Johnson syndrome have been associated with the administration of oral albuterol sulfate in children.

PRECAUTIONS

General

Albuterol tablets, as with all sympathomimetic amines, should be used with caution in patients with cardiovascular disorders, especially coronary insufficiency, cardiac arrhythmias, and hypertension; in patients with convulsive disorders, hyperthyroidism, or diabetes mellitus; and in patients who are unusually responsive to sympathomimetic amines. Clinically significant changes in systolic and diastolic blood pressure have been seen in individual patients and could be expected to occur in some patients after use of any beta-adrenergic bronchodilator.
Large doses of intravenous albuterol have been reported to aggravate preexisting diabetes mellitus and ketoacidosis. As with other beta-agonists, albuterol may produce significant hypokalemia in some patients, possibly through intracellular shunting, which has the potential to produce adverse cardiovascular effects. The decrease is usually transient, not requiring supplementation.

Information for patients

The action of albuterol tablets may last up to 8 hours or longer. Albuterol tablets should not be taken more frequently than recommended. Do not increase the dose or frequency of albuterol tablets without consulting your physician. If you find that treatment with albuterol tablets becomes less effective for symptomatic relief, your symptoms get worse, and/or you need to take the product more frequently than usual, you should seek medical attention immediately. While you are taking albuterol tablets, other asthma medications and inhaled drugs should be taken only as directed by your physician. Common adverse effects include palpitations, chest pain, rapid heart rate, and tremor or nervousness. If you are pregnant or nursing, contact your physician about use of albuterol tablets. Effective and safe use of albuterol tablets includes an understanding of the way that it should be administered.

Drug interactions

The concomitant use of albuterol tablets and other oral sympathomimetic agents is not recommended since such combined use may lead to deleterious cardiovascular effects. This recommendation does not preclude the judicious use of an aerosol bronchodilator of the adrenergic stimulant type in patients receiving albuterol tablets. Such concomitant use, however, should be individualized and not given on a routine basis. If regular coadministration is required, then alternative therapy should be considered.

Monamine Oxidase Inhibitors or Tricyclic Antidepressants
Albuterol tablets should be administered with extreme caution to patients being treated with monoamine oxidase inhibitors or tricyclic antidepressants, or within 2 weeks of discontinuation of such agents, because the action of albuterol tablets on the vascular system may be potentiated.

Beta-Blockers

Beta-adrenergic receptor blocking agents not only block the pulmonary effect of beta-agonists, such as albuterol tablets, but may produce severe bronchospasm in asthmatic patients. Therefore, patients with asthma should not normally be treated with beta-blockers. However, under certain circumstances, e.g., as prophylaxis after myocardial infarction, there may be no acceptable alternatives to the use of beta-adrenergic blocking agents in patients with asthma. In this setting, cardioselective beta-blockers could be considered, although they should be administered with caution.

Diuretics

The ECG changes and/or hypokalemia that may result from the administration of nonpotassium-sparing diuretics (such as loop or thiazide diuretics) can be acutely worsened by beta-agonists, especially when the recommended dose of the beta-agonist is exceeded. Although the clinical significance of these effects is not known, caution is advised in the coadministration of beta-agonists with nonpotassium-sparing diuretics.

Digoxin

Mean decreases of 16% to 22% in serum digoxin levels were demonstrated after single-dose intravenous and oral administration of albuterol, respectively, to normal volunteers who had received digoxin for 10 days. The clinical significance of these findings for patients with obstructive airway disease who are receiving albuterol and digoxin on a chronic basis is unclear. Nevertheless, it would be prudent to carefully evaluate the serum digoxin levels in patients who are currently receiving digoxin and albuterol.

Carcinogenesis, Mutagenesis, Impairment of Fertility

In a 2-year study in Sprague-Dawley rats, albuterol sulfate caused a significant dose-related increase in the incidence of benign leiomyomas of the mesovarium at dietary doses of 2, 10, and 50 mg/kg (approximately 1/2 , 3, and 15 times, respectively, the maximum recommended daily oral dose for adults on a mg/m^2basis, or, 2/5 , 2 and 10 times, respectively, the maximum recommended daily oral dose for children on a mg/m^2 basis). In another study this effect was blocked by the coadministration of propranolol, a non-selective beta-adrenergic antagonist.

In an 18-month study in CD-1 mice albuterol sulfate showed no evidence of tumorigenicity at dietary doses of up to 500 mg/kg, (approximately 65 times the maximum recommended daily oral dose for adults on an mg/m^2basis, or, approximately 50 times the maximum recommended daily oral dose for children on an mg/m^2basis). In a 22-month study in the Golden hamster, albuterol sulfate showed no evidence of tumorigenicity at dietary doses of up to 50 mg/kg, (approximately 8 times the maximum recommended daily oral dose for adults on a mg/m^2basis, or, approximately 7 times the maximum recommended daily oral dose for children on a mg/m^2basis).

Albuterol sulfate was not mutagenic in the Ames test with or without metabolic activation using tester strains S. typhimuriumTA1537, TA1538, and TA98 or E. ColiWP2, WP2uvrA, and WP67. No forward mutation was seen in yeast strain S. cerevisiaeS9 nor any mitotic gene conversion in yeast strain S. cerevisiaeJD1 with or without metabolic activation. Fluctuation assays in S. typhimuriumTA98 and E. ColiWP2, both with metabolic activation, were negative. Albuterol sulfate was not clastogenic in a human peripheral lymphocyte assay or in an AH1 strain mouse micronucleus assay at intraperitoneal doses of up to 200 mg/kg.
Reproduction studies in rats demonstrated no evidence of impaired fertility at oral doses up to 50 mg/kg (approximately 15 times the maximum recommended daily oral dose for adults on a mg/m^2basis).

Pregnancy

Teratogenic Effects

Albuterol tablets have been shown to be teratogenic in mice. A study in CD-1 mice at subcutaneous (sc) doses of 0.025, 0.25, and 2.5 mg/kg (approximately 3/1000, 3/100, and 3/10 times, respectively, the maximum recommended daily oral dose for adults on a mg/m^2basis), showed cleft palate formation in 5 of 111 (4.5%) fetuses at 0.25 mg/kg and in 10 of 108 (9.3%) fetuses at 2.5 mg/kg. The drug did not induce cleft palate formation at the lowest, 0.025 mg/kg. Cleft palate also occurred in 22 of 72 (30.5%) fetuses from females treated with 2.5 mg/kg of isoproterenol (positive control) subcutaneously (approximately 3/10 times the maximum recommended daily oral dose for adults on a mg/m^2basis).

A reproduction study in Stride Dutch rabbits revealed cranioschisis in 7 of 19 (37%) fetuses when albuterol tablets were administered orally at a 50 mg/kg dose (approximately 25 times the maximum recommended daily oral dose for adults on a mg/m^2basis).

There are no adequate and well-controlled studies in pregnant women. Albuterol tablets should be used during pregnancy only if the potential benefit justifies the potential risk to the fetus.
During worldwide marketing experience, various congenital anomalies, including cleft palate and limb defects, have been rarely reported in the offspring of patients being treated with albuterol tablets. Some of the mothers were taking multiple medications during their pregnancies. No consistent pattern of defects can be discerned and a relationship between albuterol tablets use and congenital anomalies has not been established.

Use in Labor and Delivery

Because of the potential for beta-agonist interference with uterine contractility, use of albuterol tablets for relief of bronchospasm during labor should be restricted to those patients in whom the benefits clearly outweigh the risk.
Tocolysis
Albuterol tablets have not been approved for the management of preterm labor. The benefit: risk ratio when albuterol tablets are administered for tocolysis has not been established. Serious adverse reactions, including maternal pulmonary edema, have been reported during or following treatment of premature labor with beta2-agonists, including albuterol tablets.
Nursing Mothers
It is not known whether this drug is excreted in human milk. Because of the potential for tumorigenicity shown for albuterol tablets in some animal studies, a decision should be made whether to discontinue nursing or to discontinue the drug, taking into account the importance of the drug to the mother.
Pediatric Use
Safety and effectiveness in children below 6 years of age have not been established.

ADVERSE REACTIONS

In clinical trials, the most frequent adverse reactions to albuterol tablets were:

Percent Incidence of Adverse Reactions

Reaction Incidence | Percent
Central nervous system
Nervousness | 20%
Tremor | 20%
Headache | 7%
Sleeplessness | 2%
Weakness | 2%
Dizziness | 2%
Drowsiness | <1%
Restlessness | <1%
Irritability | <1%
Cardiovascular
Tachycardia | 5%
Palpitations | 5%
Chest discomfort | <1%
Flushing | <1%
Musculoskeletal
Muscle cramps | 3%
Gastrointestinal
Nausea | 2%
Genitourinary
Difficulty in micturition | <1%

Rare cases of urticaria, angioedema, rash, bronchospasm and oropharyngeal edema have been reported after the use of albuterol tablets.

In addition, albuterol tablets, like other sympathomimetic agents, can cause adverse reactions such as hypertension, angina, vomiting, vertigo, central nervous system stimulation, unusual taste, and drying or irritation of the oropharynx.
The reactions are generally transient in nature, and it is usually not necessary to discontinue treatment with albuterol tablets. In selected cases, however, dosage may be reduced temporarily; after the reaction has subsided, dosage should be increased in small increments to the optimal dosage.

To report SUSPECTED ADVERSE REACTIONS, contact Rising Pharma Holdings, Inc. at 1-844-874-7464 or FDA at 1-800-FDA-1088 or www.fda.gov/medwatch.

OVERDOSAGE

The expected symptoms with overdosage are those of excessive beta-adrenergic stimulation and/or occurrence or exaggeration of any of the symptoms listed under ADVERSE REACTIONS, e.g., seizures, angina, hypertension or hypotension, tachycardia with rates up to 200 beats/min, arrhythmias, nervousness, headache, tremor, dry mouth, palpitation, nausea, dizziness, fatigue, malaise, and sleeplessness. Hypokalemia may also occur. As with all sympathomimetic medications, cardiac arrest and even death may be associated with abuse of albuterol tablets. Treatment consists of discontinuation of albuterol tablets together with appropriate symptomatic therapy. The judicious use of a cardioselective beta-receptor blocker may be considered, bearing in mind that such medication can produce bronchospasm. There is insufficient evidence to determine if dialysis is beneficial for overdosage of albuterol tablets. The oral median lethal dose of albuterol sulfate in mice is greater than 2000 mg/kg (approximately 250 times the maximum recommended daily oral dose for adults on a mg/m^2basis, or, approximately 200 times the maximum recommended daily oral dose for children on a mg/m^2basis). In mature rats, the subcutaneous (sc) median lethal dose of albuterol sulfate is approximately 450 mg/kg (approximately 110 times the maximum recommended daily oral dose for adults on a mg/m^2basis, and approximately 90 times the maximum recommended daily oral dose for children on a mg/m^2basis). In small young rats, the subcutaneous median lethal dose is approximately 2000 mg/kg (approximately 500 times the maximum recommended daily oral dose for adults on a mg/m^2basis, or, approximately 400 times the maximum recommended daily oral dose for children on a mg/m^2basis).

DOSAGE & ADMINISTRATION

The following dosages of albuterol tablets are expressed in terms of albuterol base.
Usual Dosage
Adults and Children Over 12 Years of Age
The usual starting dosage for adults and children 12 years and older is 2 or 4 mg three or four times a day.
Children 6 to 12 Years of Age:
The usual starting dosage for children 6 to 12 years age is 2 mg three or four times a day.
Dosage Adjustment
Adults and Children Over 12 Years of Age
For adults and children 12 years and older, a dosage above 4 mg four times a day should be used onlywhen the patient fails to respond. If a favorable response does not occur with the 4 mg initial dosage, it should be cautiously increased stepwise up to a maximum of 8 mg four times a day as tolerated.
Children 6 to 12 Years of Age Who Fail to Respond to the Initial Starting Dosage of 2 mg Four Times a Day
For children from 6 to 12 years of age who fail to respond to the initial starting dosage of 2 mg four times a day, the dosage may be cautiously increased stepwise, but not to exceed 24 mg/day (given in divided doses).
Elderly Patients and Those Sensitive to Beta-adrenergic Stimulators
An initial dosage of 2 mg three or four times a day is recommended for elderly patients and for those with a history of unusual sensitivity to beta-adrenergic stimulators. If adequate bronchodilation is not obtained, dosage may be increased gradually to as much as 8 mg three or four times a day.
The total daily dose should not exceed 32 mg in adults and children over 12 years and older.

HOW SUPPLIED

Albuterol Tablets, USP containing 4 mg albuterol as the sulfate are white, round shaped, scored tablets debossed with “AC 4” on one side and plain on other side.

- NDC 63629-2611-1: 20 TABLETs in a BOTTLE
- NDC 63629-2611-2: 30 TABLETs in a BOTTLE
- NDC 63629-2611-3: 60 TABLETs in a BOTTLE

Repackaged/Relabeled by:
Bryant Ranch Prepack, Inc.
Burbank, CA 91504

PACKAGE LABEL

Albuterol 4mg Tablet